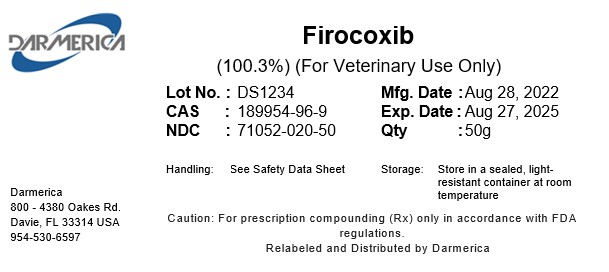 DRUG LABEL: Firocoxib
NDC: 71052-020 | Form: POWDER
Manufacturer: DARMERICA, LLC
Category: other | Type: BULK INGREDIENT - ANIMAL DRUG
Date: 20241220

ACTIVE INGREDIENTS: FIROCOXIB 1 kg/1 kg

Firocoxib